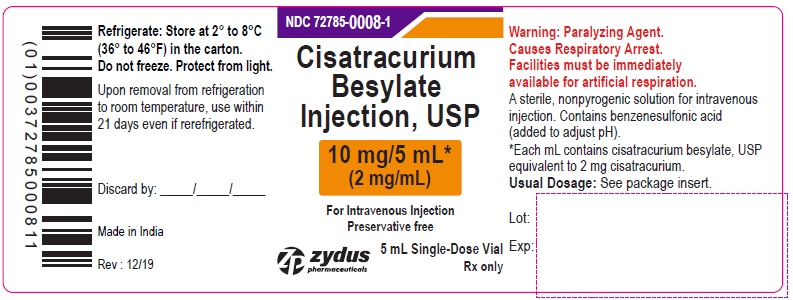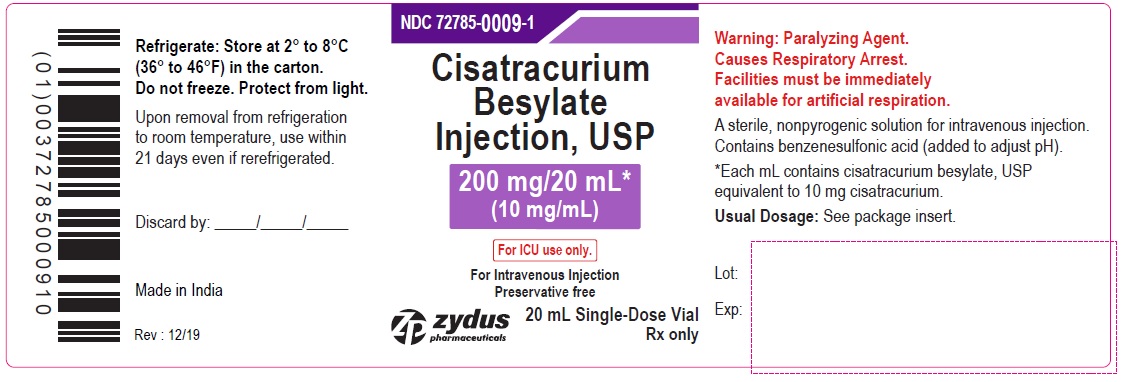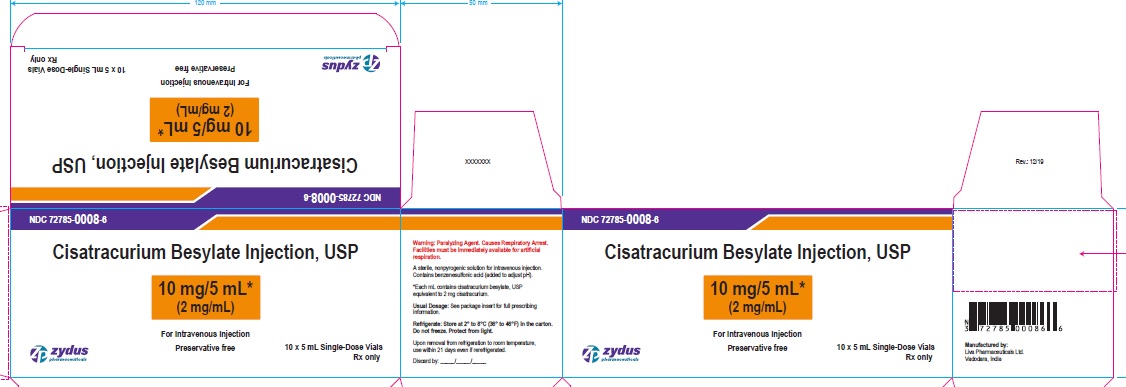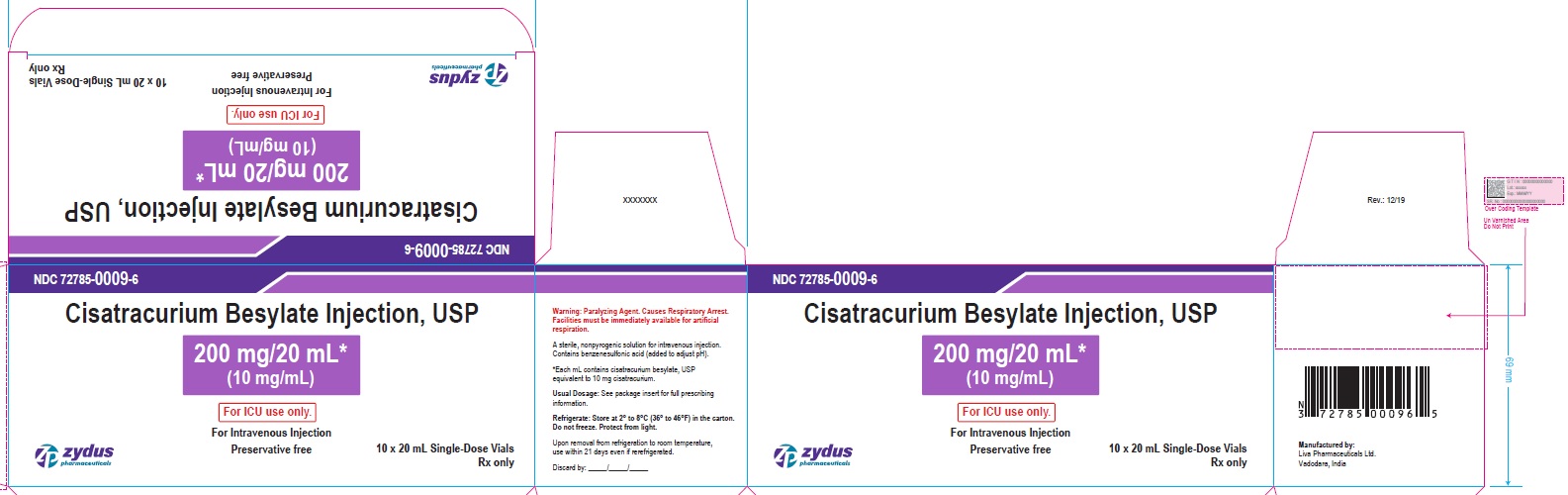 DRUG LABEL: cisatracurium besylate
NDC: 72785-0008 | Form: INJECTION
Manufacturer: Zydus Lifesciences Limited
Category: prescription | Type: HUMAN PRESCRIPTION DRUG LABEL
Date: 20221105

ACTIVE INGREDIENTS: CISATRACURIUM BESYLATE 2 mg/1 mL
INACTIVE INGREDIENTS: BENZENESULFONIC ACID; WATER

CISATRACURIUM BESYLATE INJECTION

PACKAGE LABEL

Principal Display Panel – Container Label (10 mg/5 mL)

NDC 72785-0008-1

Cisatracurium Besylate Injection, USP

10 mg/5 mL*

(2 mg/mL)

WARNING: Paralyzing Agent

For Intravenous Injection

Preservative free

5 mL Single-Dose Vial

Rx only

Zydus Pharmaceuticals

Principal Display Panel – Container Label (200 mg/20 mL)

NDC 72785-0009-1

Cisatracurium Besylate Injection, USP

200 mg/20 mL*

(10 mg/mL)

WARNING: Paralyzing Agent

For ICU use only.

For Intravenous Injection

Preservative free

20 mL Single-Dose Vial

Rx only

Zydus Pharmaceuticals

Principal Display Panel – Carton Label (10 mg/5 mL)

NDC 72785-0008-6

Cisatracurium Besylate Injection, USP

10 mg/5 mL*

(2 mg/mL)

WARNING: Paralyzing Agent

For Intravenous Injection

Preservative free

10 x 5 mL Single-Dose Vials

Rx only

Zydus Pharmaceuticals

Principal Display Panel – Carton Label (200 mg/20 mL)

NDC 72785-0009-6

Cisatracurium Besylate Injection, USP

200 mg/20 mL*

(10 mg/mL)

WARNING: Paralyzing Agent

For ICU use only.

For Intravenous Injection

Preservative free

10 x 20 mL Single-Dose Vials

Rx only

Zydus Pharmaceuticals